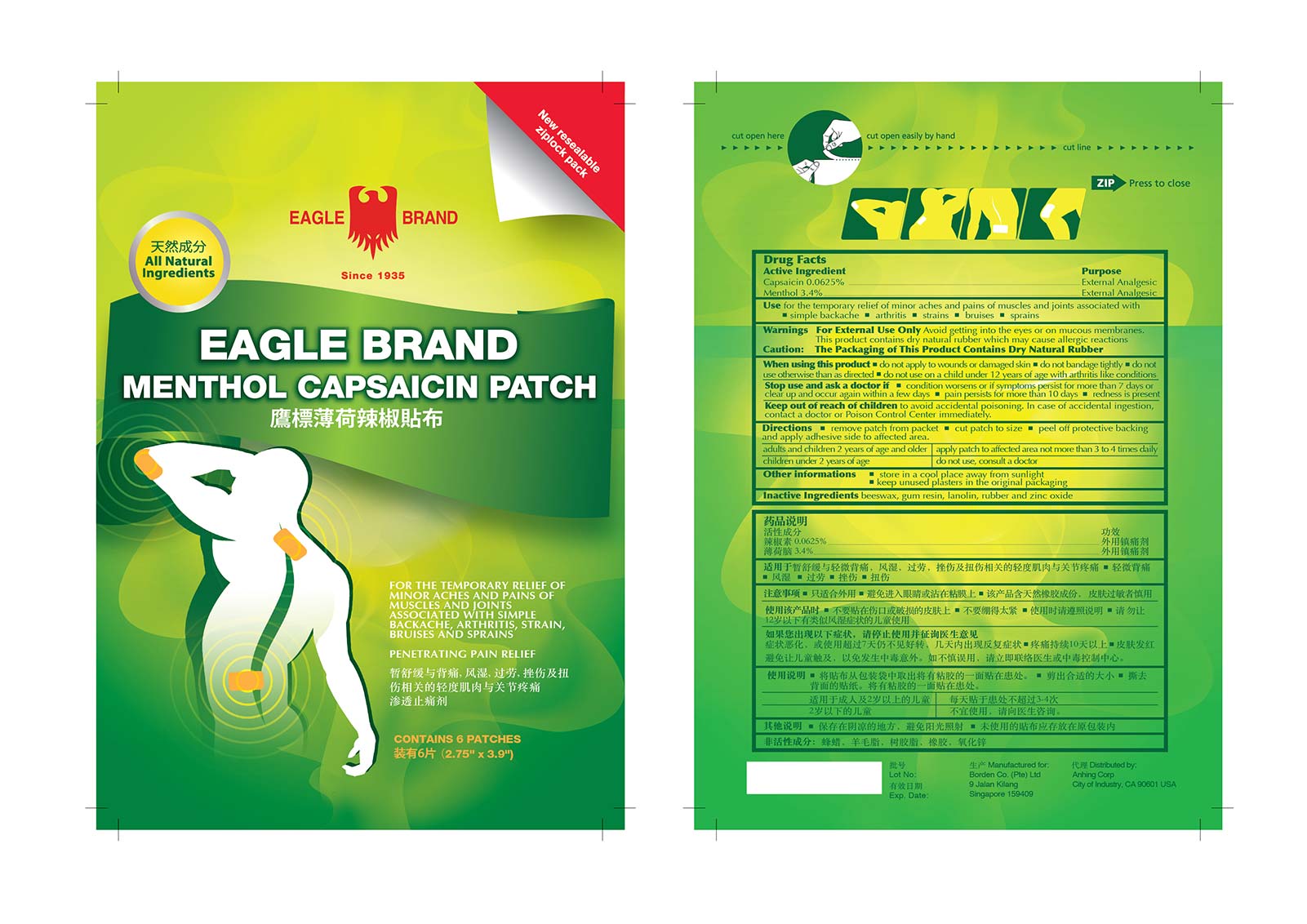 DRUG LABEL: Eagle
NDC: 42217-300 | Form: PATCH
Manufacturer: Henan Lingrui Pharmaceutical Co Ltd
Category: otc | Type: HUMAN OTC DRUG LABEL
Date: 20160826

ACTIVE INGREDIENTS: CAPSAICIN 0.0625 g/1 1; MENTHOL 3.4 g/1 1
INACTIVE INGREDIENTS: BOSWELLIA SACRA WHOLE; LANOLIN; YELLOW WAX; NATURAL LATEX RUBBER; ZINC OXIDE

Drug Facts

Active Ingredients

Capsaicin 0.0625%

Menthol 3.4%

Purpose

External Analgesic

External Analgesic

Uses

for the temporarily relief of minor pains and aches of muscles and joints associated with ■ simple backache ■ arthritis ■ strains

■ bruises ■ sprains

Warnings

For external use only Avoid getting into the eyes or on mucous membranes. This product containsdry natural rubber which may cause allergic reactions

Caution: The Packaging of this product Contains Dry Natural Rubber

When using this product

■ do not appply to wounds or damaged skin ■ do not bandage tightly ■ do not use otherwise than as directed ■ do not use on children under 12 years of age with arthritis like conditions

Stop use and ask a doctor if

■ condition worsens or symptoms persist for more than 7 days or clear up and occur again within a few days ■ pain persists for more than 10 days ■ redness is present

Keep out of reach of children

to avoid accidental poisoning. In case of accidental ingestion, contact a doctor or Poison Control Center immediately

Directions

■ remove patch from packet ■ cut patch to size ■ peel off protective backing and apply adhesive side to affected area

adults and children 2 years of age and older apply to affected area not more than 3 to 4 times daily

children under 2 years of age do not use, consult a doctor

Other Information

■ store in a cool place away from sunlight

■ keep unused plasters in the original packaging

Inactive Ingredients

beeswax, gum resin, lanolin, rubber and zinc oxide